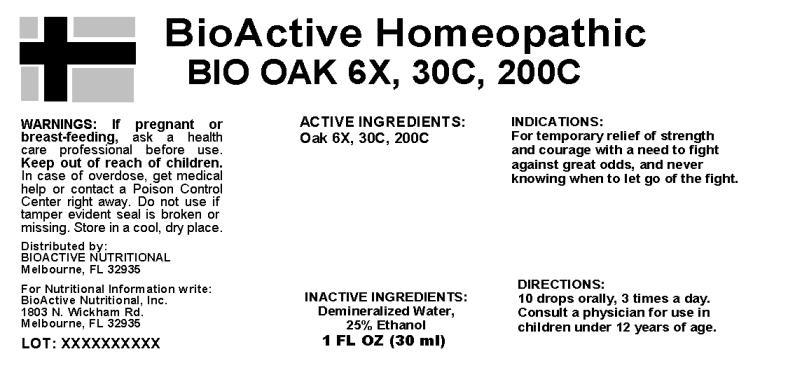 DRUG LABEL: Bio Oak
NDC: 43857-0118 | Form: LIQUID
Manufacturer: BioActive Nutritional, Inc.
Category: homeopathic | Type: HUMAN OTC DRUG LABEL
Date: 20241003

ACTIVE INGREDIENTS: QUERCUS ALBA BARK 6 [hp_X]/1 mL
INACTIVE INGREDIENTS: WATER; ALCOHOL

DRUG FACTS:

ACTIVE INGREDIENTS:

Oak 6X, 30C, 200C

INDICATIONS:

For temporary relief of strength and courage with a need to fight against great odds, and never knowing when to let go of the fight.

WARNINGS:

If pregnant or breast-feeding, ask a health care professional before use.

Keep out of reach of children. In case of overdose, get medical help or contact a Poison Control Center right away.

Do not use if tamper evident seal is broken or missing.

Store in cool, dry place.

DIRECTIONS:

10 drops orally, 3 times a day. Consult a physician for use in children under 12 years of age.

INACTIVE INGREDIENTS:

Demineralized Water, 25% Ethanol.

Keep out of reach of children. In case of overdose, get medical help or contact a Poison Control Center right away.

INDICATIONS:

For temporary relief of strength and courage with a need to fight against great odds, and never knowing when to let go of the fight.

QUESTIONS:

Distributed by:

BIOACTIVE NUTRITIONAL

Melbourne, FL 32935

For Nutritional Information write:

BioActive Nutritional, Inc.

1803 N. Wickham Rd.

Melbourne, FL 32935

PACKAGE LABEL DISPLAY:

BioActive Homeopathic

BIO OAK 6X, 30C, 200C

1 FL OZ (30 ml)